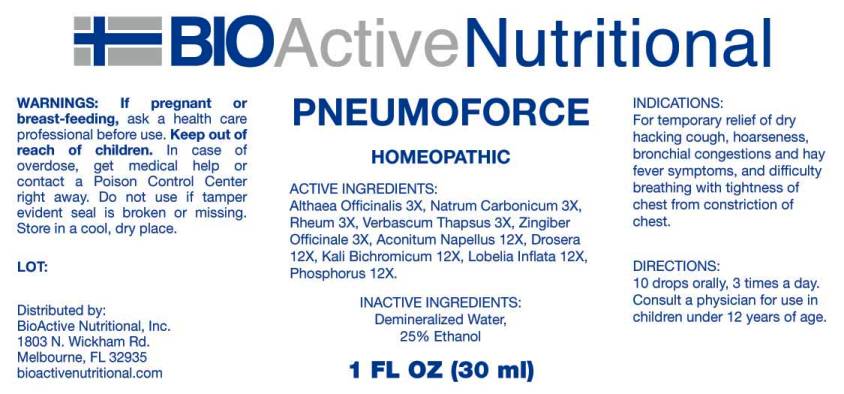 DRUG LABEL: Pneumoforce
NDC: 43857-0551 | Form: LIQUID
Manufacturer: BioActive Nutritional, Inc.
Category: homeopathic | Type: HUMAN OTC DRUG LABEL
Date: 20231130

ACTIVE INGREDIENTS: ALTHAEA OFFICINALIS ROOT 3 [hp_X]/1 mL; SODIUM CARBONATE 3 [hp_X]/1 mL; RHEUM PALMATUM ROOT 3 [hp_X]/1 mL; VERBASCUM THAPSUS WHOLE 3 [hp_X]/1 mL; GINGER 3 [hp_X]/1 mL; ACONITUM NAPELLUS WHOLE 12 [hp_X]/1 mL; DROSERA ROTUNDIFOLIA WHOLE 12 [hp_X]/1 mL; POTASSIUM DICHROMATE 12 [hp_X]/1 mL; LOBELIA INFLATA WHOLE 12 [hp_X]/1 mL; PHOSPHORUS 12 [hp_X]/1 mL
INACTIVE INGREDIENTS: WATER; ALCOHOL

DRUG FACTS:

ACTIVE INGREDIENTS:

Althaea Officinalis 3X, Natrum Carbonicum 3X, Rheum (Palmatum) 3X, Verbascum Thapsus 3X, Zingiber Officinale 3X, Aconitum Napellus 12X, Drosera Rotundifolia 12X, Kali Bichromicum 12X, Lobelia Inflata 12X, Phosphorus 12X.

INDICATIONS:

For temporary relief of dry hacking cough, hoarseness, bronchial congestions and hay fever symptoms, and difficulty breathing with tightness of chest from constriction of chest.

WARNINGS:

If pregnant or breast-feeding, ask a health care professional before use.

Keep out of reach of children. In case of overdose, get medical help or contact a Poison Control Center right away.

Do not use if tamper evident seal is broken or missing.

Store in cool, dry place.

KEEP OUT OF REACH OF CHILDREN:

In case of overdose, get medical help or contact a Poison Control Center right away.

DIRECTIONS:

10 drops orally, 3 times a day. Consult a physician for use in children under 12 years of age.

INDICATIONS:

For temporary relief of dry hacking cough, hoarseness, bronchial congestions and hay fever symptoms, and difficulty breathing with tightness of chest from constriction of chest.

INACTIVE INGREDIENTS:

Demineralized Water, 25% Ethanol.

QUESTIONS:

Distributed by:
BioActive Nutritional, Inc.
1803 N. Wickham Rd.
Melbourne, FL 32935
bioactivenutritional.com

PACKAGE LABEL DISPLAY:

BIOActive Nutritional

PNEUMOFORCE

HOMEOPATHIC

1 FL OZ (30 ml)